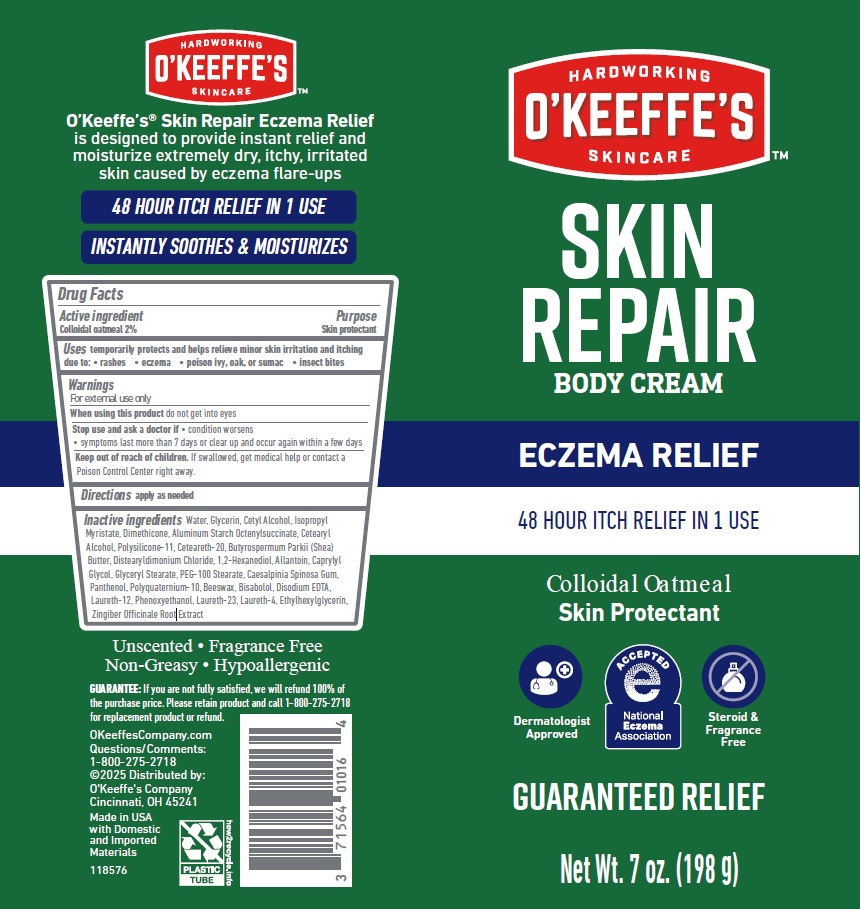 DRUG LABEL: OKeeffes Skin Repair
NDC: 71564-010 | Form: CREAM
Manufacturer: The Gorilla Glue Company/O'Keeffe's Company
Category: otc | Type: HUMAN OTC DRUG LABEL
Date: 20250901

ACTIVE INGREDIENTS: OATMEAL 2 g/100 g
INACTIVE INGREDIENTS: CAPRYLYL GLYCOL; LAURETH-12; CAESALPINIA SPINOSA RESIN; POLYQUATERNIUM-10 (1000 MPA.S AT 2%); YELLOW WAX; PEG-100 STEARATE; LAURETH-23; PHENOXYETHANOL; ETHYLHEXYLGLYCERIN; 1,2-HEXANEDIOL; EDETATE DISODIUM; GINGER; SHEA BUTTER; ALLANTOIN; WATER; GLYCERIN; CETYL ALCOHOL; ISOPROPYL MYRISTATE; DIMETHICONE; ALUMINUM STARCH OCTENYLSUCCINATE; CETOSTEARYL ALCOHOL; POLYOXYL 20 CETOSTEARYL ETHER; DISTEARYLDIMONIUM CHLORIDE; PANTHENOL; LEVOMENOL; DIMETHICONE/VINYL DIMETHICONE CROSSPOLYMER (SOFT PARTICLE); GLYCERYL MONOSTEARATE; LAURETH-4

OKeeffes Skin Repair Body Cream Eczema Relief

Drug Facts

Active ingredient

Colloidal oatmeal 2%

Purpose

Skin protectant

Uses

temporarily protects and helps relieve minor skin irritation and itching due to:

- rashes
- eczema
- poison ivy, oak, or sumac
- insect bites

Warnings

For external use only

When using this product do not get into eyes

Stop use and ask a doctor if

- condition worsens
- symptoms last more than 7 days or clear up and occur again within a few days

Keep out of reach of children. If swallowed, get medical help or contact a Poison Control Center right away.

Directions

apply as needed

INACTIVE INGREDIENT

Inactive ingredients Water, Glycerin, Cetyl Alcohol, Isopropyl Myristate, Dimethicone, Aluminum Starch Octenylsuccinate, Cetearyl Alcohol, Polysilicone-11, Ceteareth-20, Butyrospermum Parkii (Shea) Butter, Distearyldimonium Chloride, 1,2-Hexanediol, Allantoin, Caprylyl Glycol, Glyceryl Stearate, PEG-100 Stearate, Caesalpinia Spinosa Gum, Panthenol, Polyquaternium-10, Beeswax, Bisabolol, Disodium EDTA, Laureth-12, Phenoxyethanol, Laureth-23, Laureth-4, Ethylhexylglycerin, Zingiber Offcinale Root Extract

OKeeffesCompany.com

Questions/Comments: 1-800-275-2718

©2025 Distributed by:

O'Keeffe's Company

Cincinnati, OH 45241

Made in USA with Domestic and Imported Materials

PACKAGE LABEL

O'KEEFFE'S®

SKIN REPAIR BODY CREAM

ECZEMA RELIEF

48 HOUR ITCH RELIEF IN ONE USE

Colloidal Oatmeal Skin Protectant

Dermatologist Approved

ACCEPTED National Eczema Association

Steroid & Fragrance Free

GUARANTEED RELIEF

Net Wt. 7 oz. (198 g)